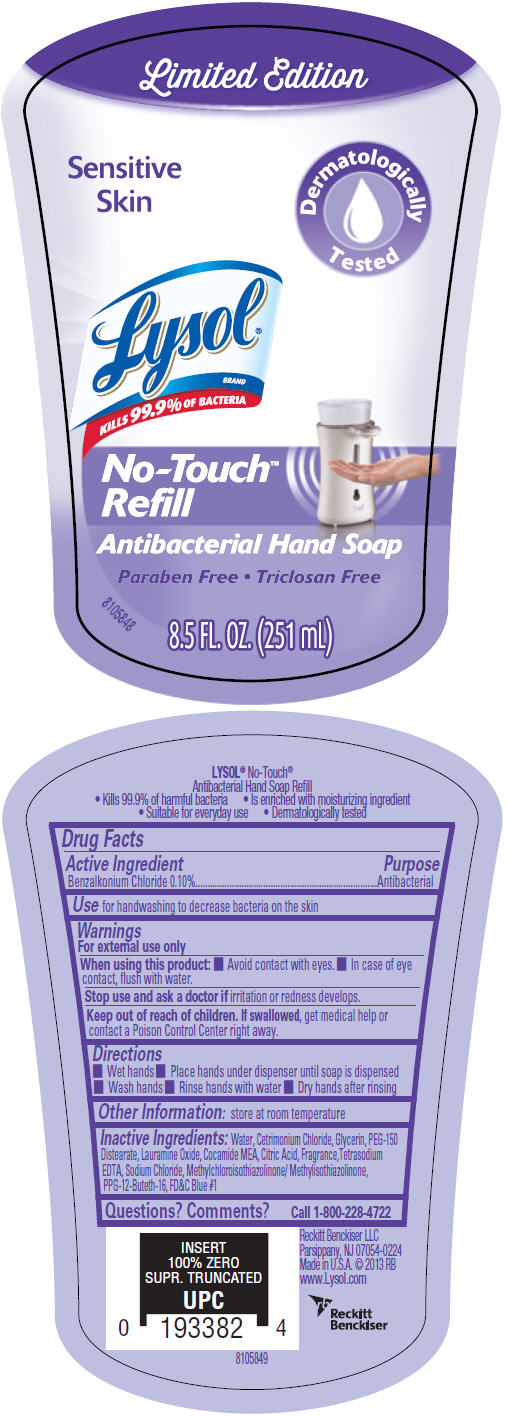 DRUG LABEL: Lysol 
NDC: 63824-479 | Form: SOLUTION
Manufacturer: Reckitt Benckiser LLC
Category: otc | Type: HUMAN OTC DRUG LABEL
Date: 20131203

ACTIVE INGREDIENTS: Benzalkonium Chloride 0.1 g/100 mL
INACTIVE INGREDIENTS: Water; Cetrimonium Chloride; Glycerin; PEG-150 Distearate; Lauramine Oxide; Coco Monoethanolamide; Citric Acid Monohydrate; Edetate Sodium; Sodium Chloride; Methylchloroisothiazolinone; Methylisothiazolinone; PPG-12-Buteth-16; FD&C Blue No. 1

Lysol®
No-Touch™ Antibacterial Hand Soap

Drug Facts

Active Ingredient

Benzalkonium Chloride 0.10%

Purpose

Antibacterial

Use

for handwashing to decrease bacteria on the skin

Warnings

For external use only

When using this product

- Avoid contact with eyes.
- In case of eye contact, flush with water.

Stop use and ask a doctor if irritation or redness develops.

Keep out of reach of children. If swallowed, get medical help or contact a Poison Control Center right away.

Directions

- Wet hands
- Place hands under dispenser until soap is dispensed
- Wash hands
- Rinse hands with water
- Dry hands after rinsing

Other Information

store at room temperature

Inactive Ingredients

Water, Cetrimonium Chloride, Glycerin, PEG-150 Distearate, Lauramine Oxide, Cocamide MEA, Citric Acid, Fragrance,Tetrasodium EDTA, Sodium Chloride, Methylchloroisothiazolinone/ Methylisothiazolinone, PPG-12-Buteth-16, FD&C Blue #1

Questions? Comments?

Call 1-800-228-4722

Made in U.S.A.

PRINCIPAL DISPLAY PANEL - 251 mL Bottle Label

Limited Edition

Sensitive
Skin

Dermatologically
Tested

Lysol®
BRAND
KILLS 99.9% OF BACTERIA

No-Touch™
Refill

Antibacterial Hand Soap

Paraben Free • Triclosan Free

8.5 FL. OZ. (251 mL)

8105848